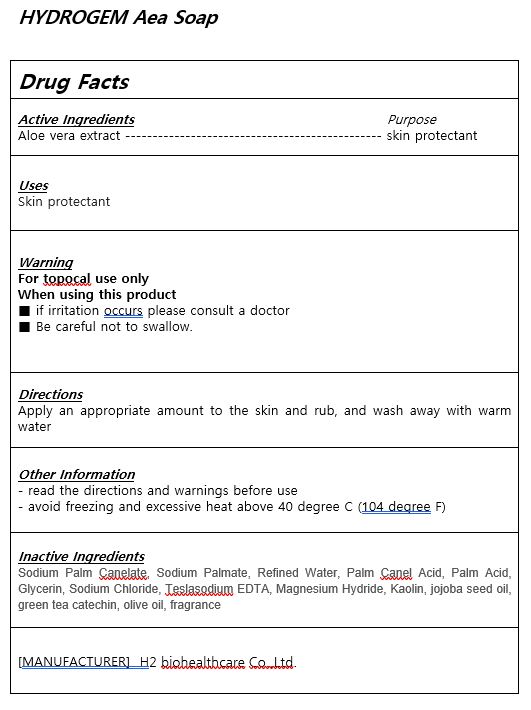 DRUG LABEL: HYDROGEM AeaSoap
NDC: 83811-0002 | Form: SOAP
Manufacturer: H2 biohealthcare Co.,Ltd
Category: otc | Type: HUMAN OTC DRUG LABEL
Date: 20231119

ACTIVE INGREDIENTS: ALOE VERA LEAF 5 g/100 g
INACTIVE INGREDIENTS: KAOLIN; WATER

ACTIVE INGREDIENT

aloe very extract

PURPOSE

skin protectant

Keep out of reach of children

INDICATIONS AND USAGE

Apply an appropriate amount to the skin and rub, and wash away with warm water

WARNINGS

For topical use only

■ if irritation occurs please consult a doctor

■ Be careful not to swallow.

INACTIVE INGREDIENT

Sodium Palm Canelate, Sodium Palmate, Refined Water, Palm Canel Acid, Palm Acid, Glycerin, Sodium Chloride, Teslasodium EDTA, Magnesium Hydride, Kaolin, jojoba seed oil, green tea catechin, olive oil, fragrance

DOSAGE AND ADMINISTRATION

For topical use only